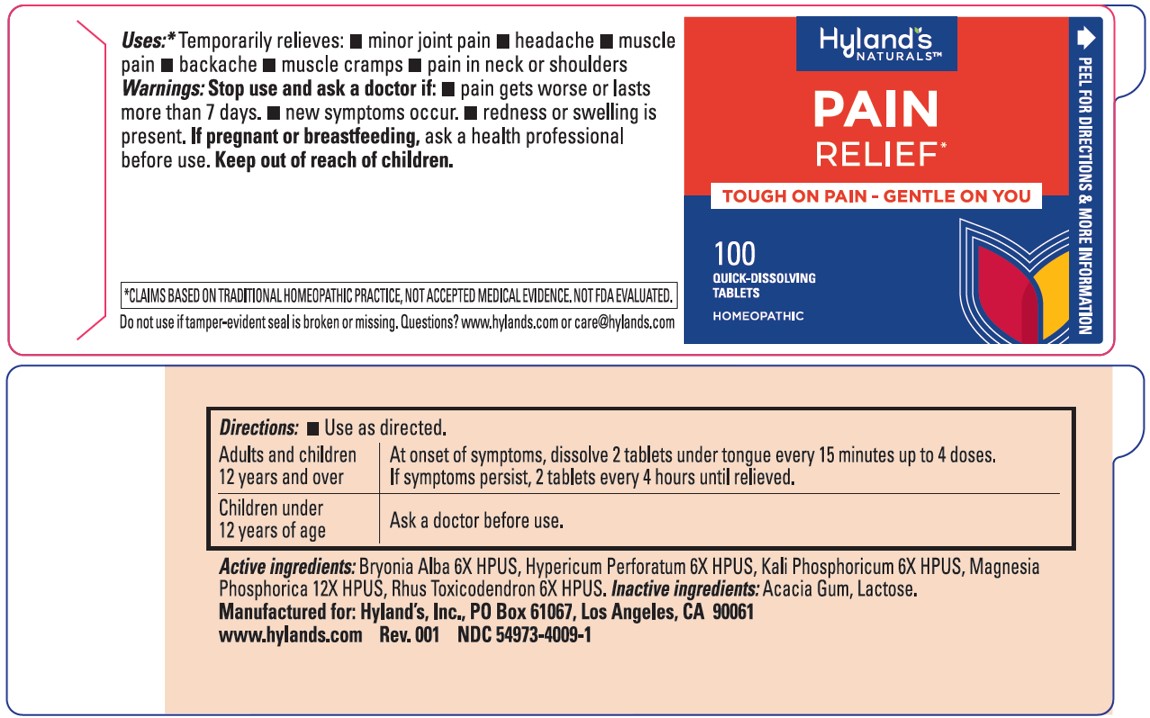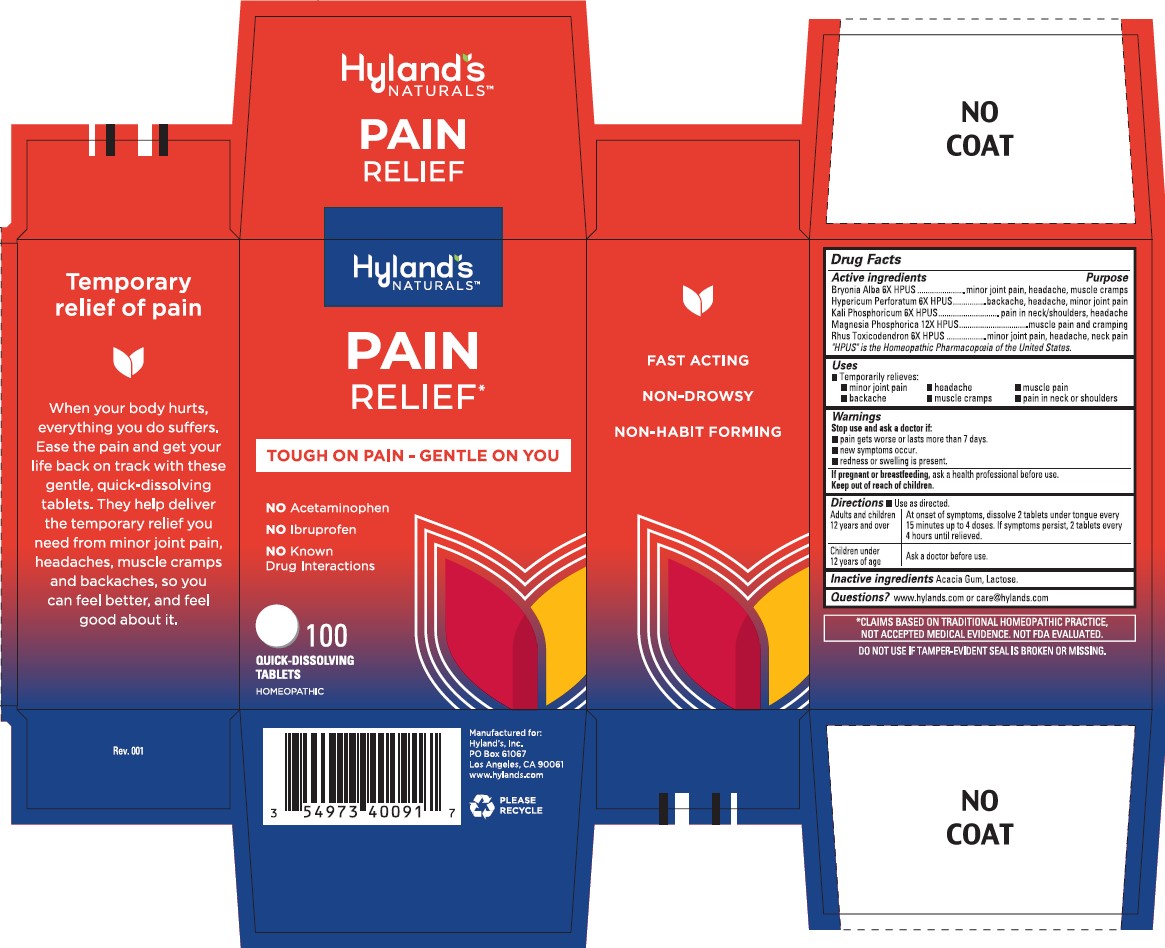 DRUG LABEL: Pain Relief
NDC: 54973-4009 | Form: TABLET
Manufacturer: Hyland's Inc.
Category: homeopathic | Type: HUMAN OTC DRUG LABEL
Date: 20230508

ACTIVE INGREDIENTS: MAGNESIUM PHOSPHATE, DIBASIC TRIHYDRATE 12 [hp_X]/1 1; TOXICODENDRON PUBESCENS LEAF 6 [hp_X]/1 1; DIBASIC POTASSIUM PHOSPHATE 6 [hp_X]/1 1; BRYONIA ALBA ROOT 6 [hp_X]/1 1; HYPERICUM PERFORATUM 6 [hp_X]/1 1
INACTIVE INGREDIENTS: LACTOSE MONOHYDRATE; ACACIA

Hyland's Naturals Pain Relief

PURPOSE

Pain Relief

Drug Facts

Active ingredients

Active ingredients | Purpose
Bryonia Alba 6X HPUS | minor joint pain, headache, muscle cramps
Hypericum Perforatum 6X HPUS | backache, headache, minor joint pain
Kali Phosphoricum 6X HPUS | pain in neck/shoulders, headache
Magnesia Phosphorica 12X HPUS | muscle pain, backache
Rhus Toxicodendron 6X HPUS | minor joint pain, headache, neck pain

"HPUS" indicates that the active ingredients are in the official Homeopathic

Pharmacopoeia of the United States.

Warnings

Stop use and ask a doctor if

■ pain gets worse or lasts more than 7 days.
■ new symptoms occur.
■ redness or swelling is present.

If pregnant or breastfeeding

Ask a health professional before use.

Directions

■ Use as directed.

Adults and children 12 years and over | At onset of symptoms, dissolve 2 tablets under tongue every 15 minutes up to 4 doses. If symptoms persist, 2 tablets every 4 hours until relieved.
Children under 12 years of age | Ask a doctor before use.

Inactive ingredients

Acacia Gum, Lactose.

Questions?

www.hylands.com or care@hylands.com

Indications and Usage

(Uses)

Update "Temporarily relieves symptoms of pain, including:" to "Temporarily relieves:"

Removed extra bullets

Dosage and Administration

(Directions)

■ Use as directed

Adults and children 12 years and over | At onset of symptoms, dissolve 2 tablets under tongue every; 15 minutes up to 4 doses. If symptoms persist, 2 tablets every 4 hours until relieved.
Children under 12 years of age | Ask a doctor before use.

Uses

■ Temporarily relieves: ■ minor joint pain ■ headache ■ muscle pain ■ backache ■ muscle cramps ■ pain in neck or shoulders

Principal Display Panel

54973-4009-01

100 Tablets